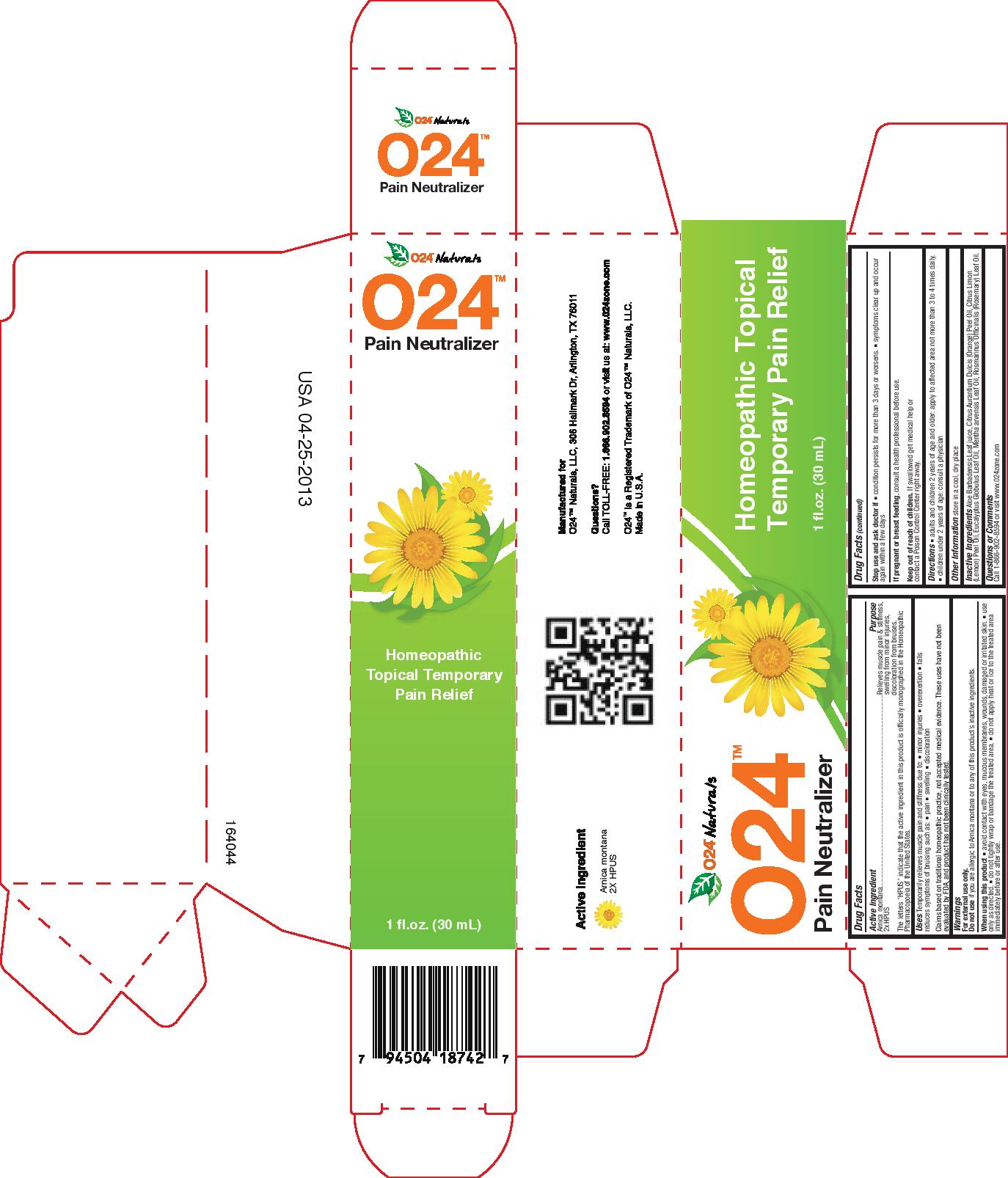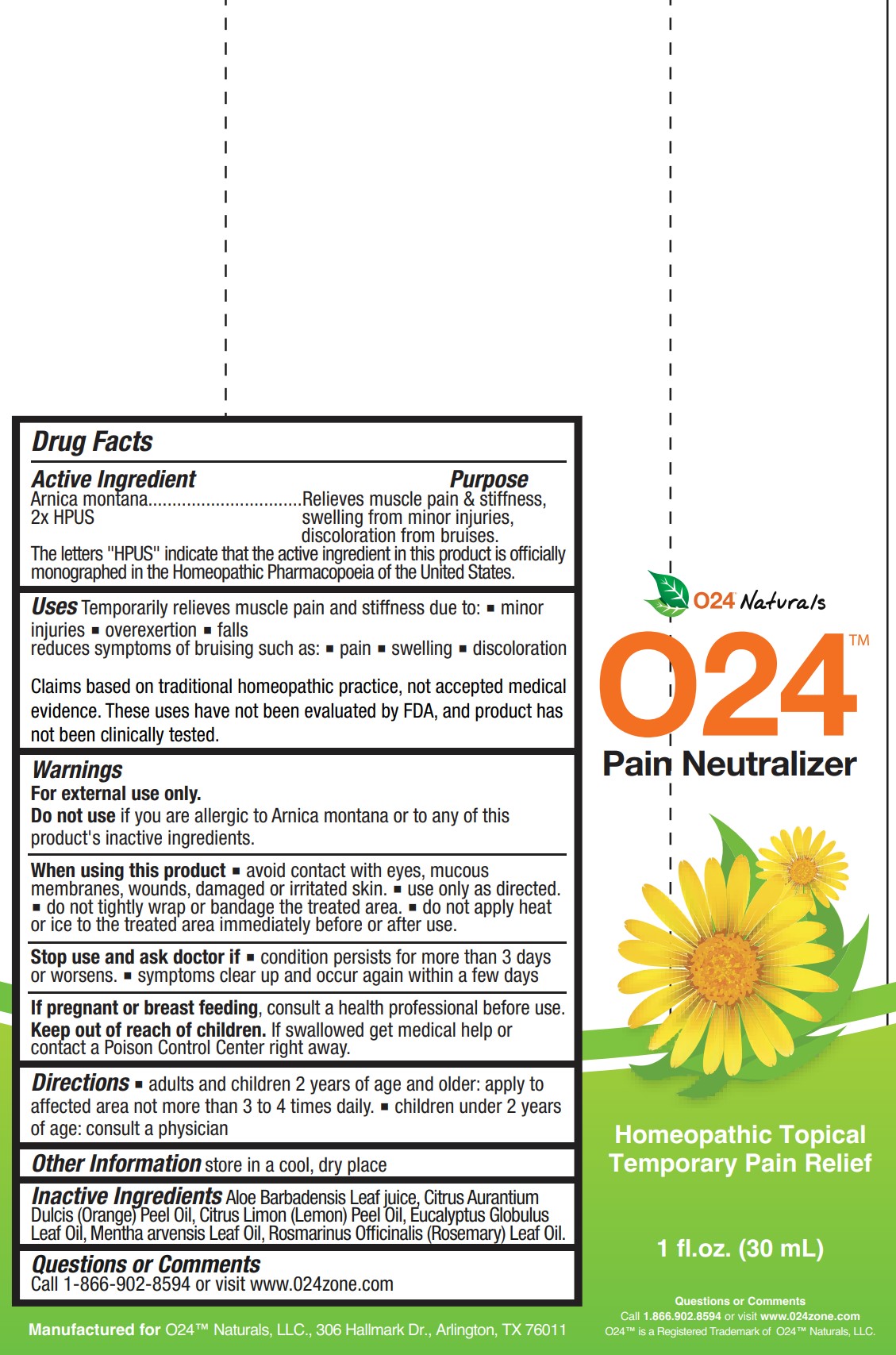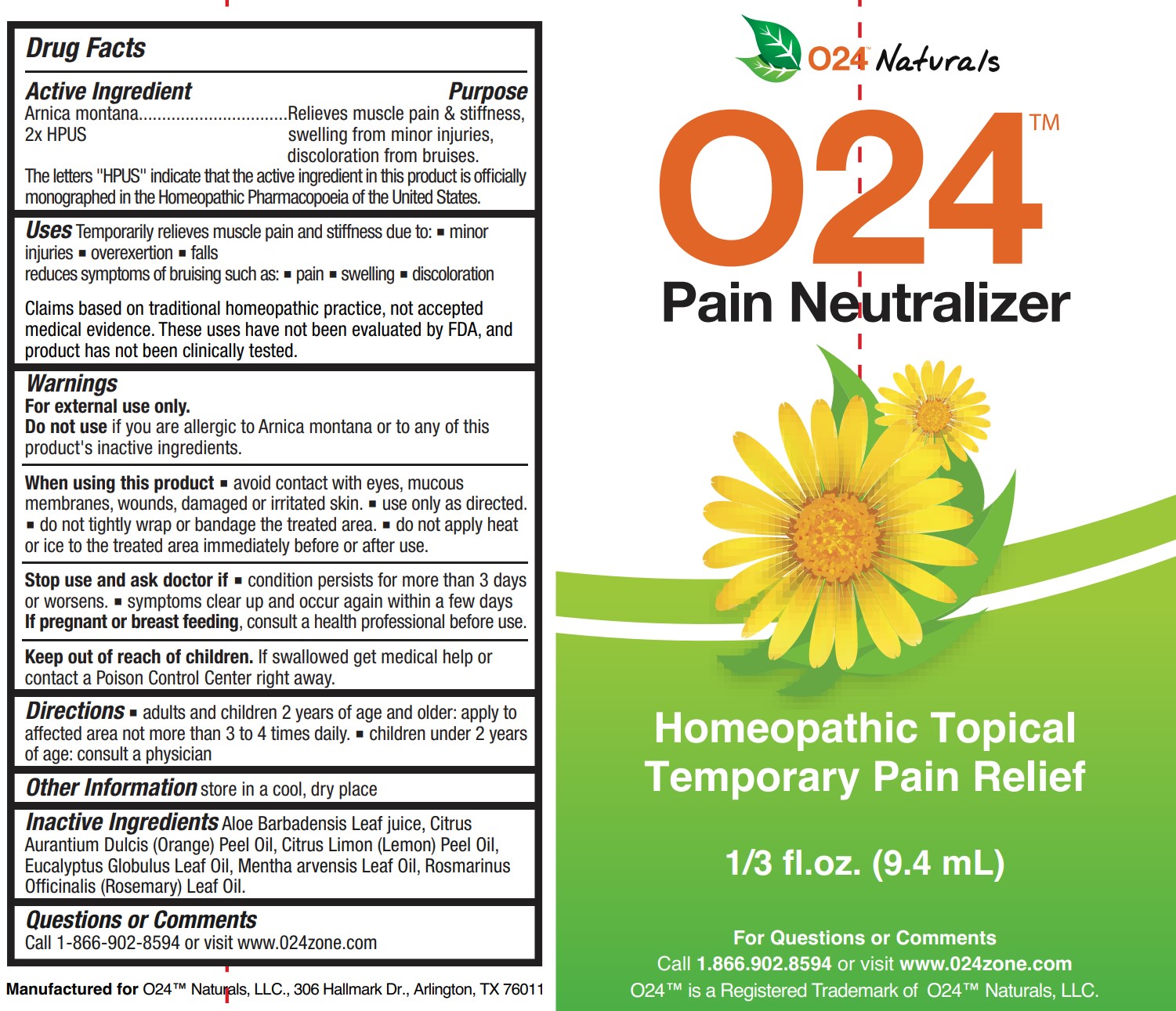 DRUG LABEL: O24 Pain Neutralizer
NDC: 58265-007 | Form: LIQUID
Manufacturer: O24 Naturals, LLC
Category: homeopathic | Type: HUMAN OTC DRUG LABEL
Date: 20230117

ACTIVE INGREDIENTS: ARNICA MONTANA 2 [hp_X]/9.4 g
INACTIVE INGREDIENTS: ORANGE OIL, COLD PRESSED; LEMON OIL, COLD PRESSED; ALOE VERA LEAF; MENTHA ARVENSIS LEAF OIL; EUCALYPTUS OIL; ROSEMARY OIL

O24 Pain Neutralizer

Active ingredient

Arnica montana 2x HPUS

Purpose

Arnica montana 2x HPUS......................Relieves muscle pain & stiffness, swelling from minor injuries, discloloration from bruises.

The letters "HPUS" indicate that the active ingredient in this product is officially monographed in the Homeopathic Pharmacopoeia of the United States.

Uses

Temporarily relieves muscle pain and stiffness due to:

- minor injuries
- overexertion
- falls

Reduces symptoms of bruising such as:

- pain
- swelling
- discloloration

Claims based on traditional homeopathic practice, not accepted medical evidence. These uses have not been evaluated by FDA, and product has not been clinically tested.

Warnings

For external use only.

Do not use if you are allergic to Arnica montana or to any of this product's inactive ingredients.

When using this product

- avoid contact with eyes, mucous membranes, wounds, damaged or irritated skin
- use only as directed
- do not tightly wrap or bandage the treated area
- do not apply heat or ice to the treated area immediately before or after use

Stop use and ask doctor if

- condition persists for more than 3 days or worsens
- symptoms clear up and occur again within a few days

PREGNANCY OR BREAST FEEDING

If pregnant or breastfeeding, consult a health professional before use.

Keep out of reach of children. If swallowed, get medical help or contact a Poison Control Center right away.

Directions

- adults and children 2 years of age and older: apply to affected area not more than 3 to 4 times daily
- children under 2 years of age: consult a physician

Other information

store in a cool, dry place

Inactive ingredients

Aloe Barbadensis Leaf juice, Citrus Aurantium Dulcis (Orange) Peel Oil, Citrus Limon (Lemon) Peel Oil, Eucalyptus Globulus Leaf Oil, Mentha arvensis Leaf Oil, Rosmarinus Officinalis (Rosemary) Leaf Oil

Questions or Comments

Call 1-866-902-8594 or visit www.024zone.com

PACKAGE LABEL

O24 Naturals

O24 Pain Neutralizer

Homeopathic Topical Temporary Pain Relief

1 fl oz (30 mL)